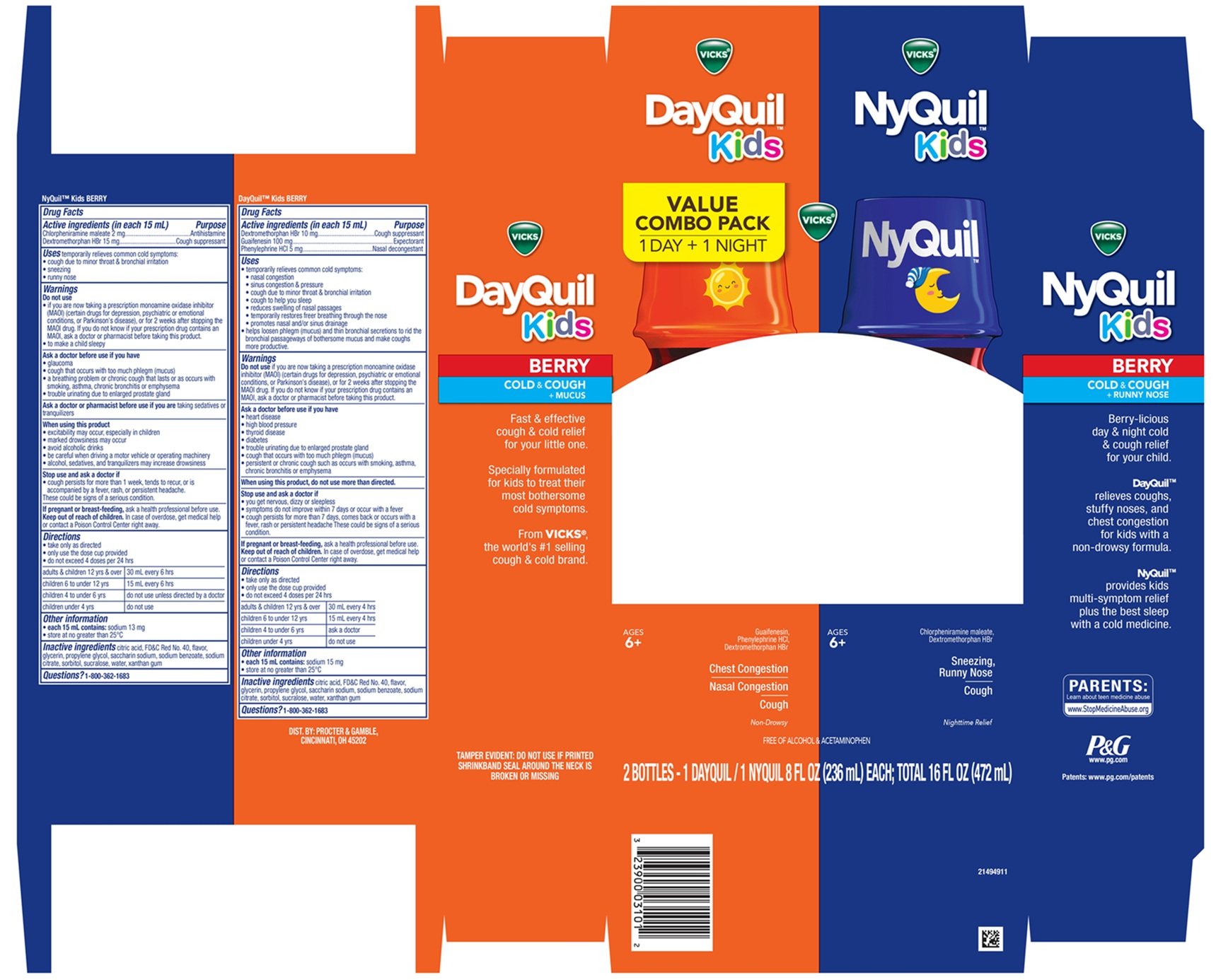 DRUG LABEL: Vicks DayQuil NyQuil BERRY Kids
NDC: 69423-780 | Form: KIT | Route: ORAL
Manufacturer: The Procter & Gamble Manufacturing Company
Category: otc | Type: HUMAN OTC DRUG LABEL
Date: 20260219

ACTIVE INGREDIENTS: GUAIFENESIN 100 mg/15 mL; PHENYLEPHRINE HYDROCHLORIDE 5 mg/15 mL; DEXTROMETHORPHAN HYDROBROMIDE 10 mg/15 mL; CHLORPHENIRAMINE MALEATE 2 mg/15 mL; DEXTROMETHORPHAN HYDROBROMIDE 15 mg/15 mL
INACTIVE INGREDIENTS: SODIUM CITRATE; SORBITOL; SUCRALOSE; FD&C RED NO. 40; ANHYDROUS CITRIC ACID; XANTHAN GUM; SODIUM BENZOATE; GLYCERIN; PROPYLENE GLYCOL; WATER; SACCHARIN SODIUM; SORBITOL; SUCRALOSE; ANHYDROUS CITRIC ACID; PROPYLENE GLYCOL; GLYCERIN; XANTHAN GUM; FD&C RED NO. 40; WATER; SACCHARIN SODIUM; SODIUM BENZOATE; SODIUM CITRATE

Vicks® DayQuil™ | NyQuil™ Kids BERRY COLD & COUGH +
Convenience Pack

VICKS ® NyQuil™ Kids BERRY COLD & COUGH + MUCUS

Drug Facts

Active ingredients (in each 15 mL)

Chlorpheniramine maleate 2 mg
Dextromethorphan HBr 15 mg

Purpose

Antihistamine
Cough suppressant

Uses

temporarily relieves common cold symptoms:

- cough due to minor throat & bronchial irritation
- sneezing
- runny nose

Warnings

Do not use

• If you are now taking a prescription monoamine oxidase inhibitor (MAOI) (certain drugs for depression, psychiatric or emotional conditions, or Parkinson's disease), or for 2 weeks after stopping the MAOI drug. If you do not know if your prescription drug contains an MAOI, ask a doctor or pharmacist before taking this product.

• to make a child sleepy

Ask a doctor before use if you have

- glaucoma
- cough that occurs with too much phlegm (mucus)
- a breathing problem or chronic cough that lasts or as occurs with smoking, asthma, chronic bronchitis or emphysema
- trouble urinating due to enlarged prostate gland

Ask a doctor or pharmacist before use if you are

taking sedatives or tranquilizers.

When using this product

- excitability may occur, especially in children
- marked drowsiness may occur
- avoid alcoholic drinks
- be careful when driving a motor vehicle or operating machinery
- alcohol, sedatives, & tranquilizers may increase drowsiness

Stop use and ask a doctor if

- cough lasts more than 1 week, tends to recur, or is accompanied by fever, rash, or persistent headache.

These could be signs of a serious condition.

If pregnant or breast-feeding,

ask a health professional before use.

Keep out of reach of children.

OVERDOSAGE

In case of overdose, get medical help or contact a Poison Control Center right away.

Directions

• take only as directed
• only use the dose cup provided
• do not exceed 4 doses per 24 hrs

adults & children 12 yrs & over | 30 mL every 6 hrs
children 6 to under 12 yrs | 15 mL every 6 hrs
children 4 to under 6 yrs | do not use unless directed by a doctor
children under 4 yrs | do not use

Other information

- each 15 mL contains:sodium 13 mg
- Store at no greater than 25°C

Inactive ingredients

citric acid, FD&C Red No. 40, flavor, glycerin, propylene glycol, saccharin sodium, sodium benzoate, sodium citrate, sorbitol, sucralose, water, xanthan gum

Questions?

1-800-362-1683

Vicks® DayQuil™ Kids BERRY COLD & COUGH + MUCUS

Drug Facts

Active ingredients (in each 15 mL)

Dextromethorphan HBr 10 mg

Guaifenesin 100 mg

Phenylephrine HCl 5 mg

Purpose

Cough suppressant
Expectorant
Nasal decongestant

Uses

- temporarily relieves common cold symptoms:
- nasal congestion
- sinus congestion & pressure
- cough due to minor throat & bronchial irritation
- cough to help you sleep
- reduces swelling of nasal passages
- temporarily restores freer breathing through the nose
- promotes nasal and/or sinus drainage
- helps loosen phlegm (mucus) and thin bronchial secretions to rid the bronchial passageways of bothersome mucus and make coughs more productive.

Warnings

Do not use if you are now taking a prescription monoamine oxidase inhibitor (MAOI) (certain drugs for depression, psychiatric or emotional conditions, or Parkinson's disease), or for 2 weeks after stopping the MAOI drug. If you do not know if your prescription drug contains an MAOI, ask a doctor or pharmacist before taking this product.

Ask a doctor before use if you have

- heart disease
- high blood pressure
- thyroid disease
- diabetes
- trouble urinating due to enlarged prostate gland
- cough that occurs with too much phlegm (mucus)
- persistent or chronic cough such as occurs with smoking, asthma, chronic bronchitis or emphysema

When using this product,

do not use more than directed.

Stop use and ask a doctor if

- you get nervous, dizzy or sleepless
- symptoms do not improve within 7 days or occur with a fever
- cough persists for more than 7 days, comes back or occurs with a fever, rash or persistent headache

These could be signs of a serious condition.

If pregnant or breast-feeding,

ask a health professional before use.

Keep out of reach of children.

OVERDOSAGE

In case of overdose, get medical help or contact a Poison Control Center right away.

Directions

• take only as directed
• only use the dose cup provided
• do not exceed 4 doses per 24 hrs

adults & children 12 yrs & over | 30 mL every 4 hrs
children 6 to under 12 yrs | 15 mL every 4 hrs
children 4 to under 6 yrs | ask a doctor
children under 4 yrs | do not use

Other information

- each 15 mL contains: sodium 15 mg
- store at no greater than 25°C

Inactive ingredients

citric acid, FD&C Red No. 40, flavor, glycerin, propylene glycol, saccharin sodium, sodium benzoate, sodium citrate, sorbitol, sucralose, water, xanthan gum

Questions?

1-800-362-1683

TAMPER EVIDENT:DO NOT USE IF PRINTED SHRINKBAND SEAL AROUND THE NECK IS BROKEN OR MISSING.

DIST. BY: PROCTER & GAMBLE, CINCINNATI, OH 45202

PRINCIPAL DISPLAY PANEL - Convenience Pack

Vicks® DayQuil™ Kids Vicks® NyQuil™ Kids

VALUE COMBO PACK

1 DAY + 1 NIGHT

VICKS ®

DayQuil™ Kids BERRY

COLD & COUGH + MUCUS

Guaifenesin, Phenylephrine HCl, Dextromethorphan HBr

Chest Congestion

Nasal Congestion
Cough
Non-Drowsy

Ages 6+

NyQuil ™ Kids BERRY

COLD & COUGH + RUNNY NOSE

Chlorpheniramine maleate, Dextromethorphan HBr

Sneezing, Runny Nose

Cough

Nighttime Relief

Ages 6+

FREE OF ALCOHOL & ACETAMINOPHEN

2 BOTTLES - 1 DAYQUIL/1 NYQUIL 8 FL OZ (236 mL) EACH; TOTAL 16 FL OZ (472 mL)